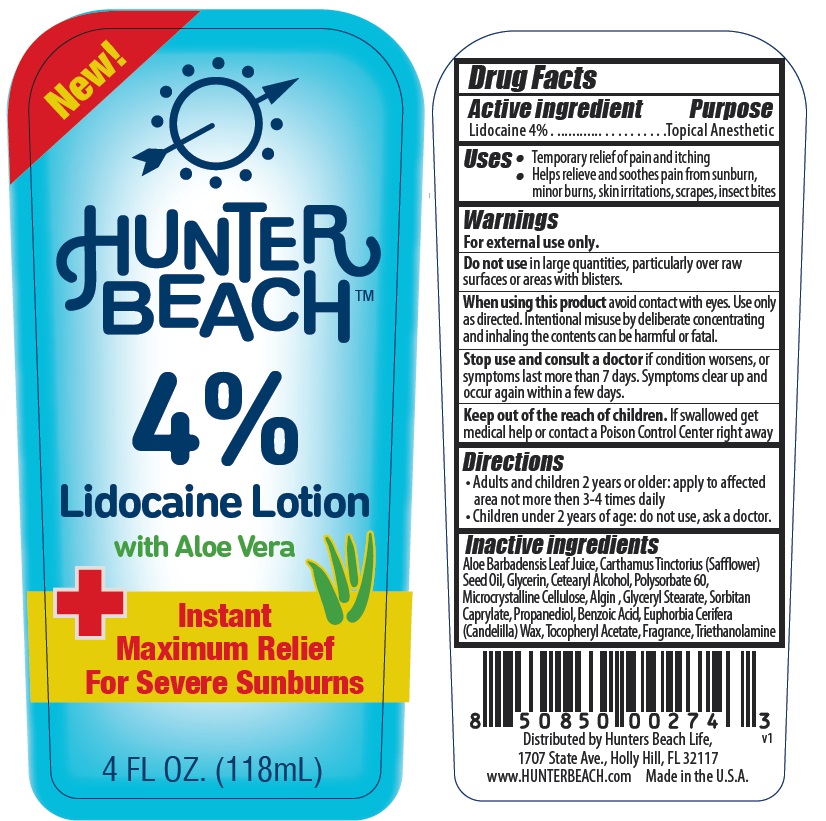 DRUG LABEL: Hunter Beach 4%
NDC: 82517-001 | Form: LOTION
Manufacturer: HUNTERS BEACH LIFE
Category: otc | Type: HUMAN OTC DRUG LABEL
Date: 20241218

ACTIVE INGREDIENTS: LIDOCAINE 4 g/100 mL
INACTIVE INGREDIENTS: ALOE VERA LEAF; SAFFLOWER OIL; GLYCERIN; CETOSTEARYL ALCOHOL; POLYSORBATE 60; MICROCRYSTALLINE CELLULOSE; SODIUM ALGINATE; GLYCERYL MONOSTEARATE; SORBITAN MONOCAPRYLATE; PROPANEDIOL; BENZOIC ACID; CANDELILLA WAX; .ALPHA.-TOCOPHEROL ACETATE; TROLAMINE

HUNTER BEACH™ 4% Lidocaine Lotion

Active ingredient

Lidocaine 4%

Purpose

Topical Anesthetic

Uses

• Temporary relief of pain and itching
• Helps relieve and soothes pain from sunburn, minor burns, skin irritations, scrapes, insect bites

Warnings

For external use only.

Do not use in large quantities, particularly over raw surfaces or areas with blisters.

When using this product avoid contact with eyes. Use only as directed. Intentional misuse by deliberate concentrating and inhaling the contents can be harmful or fatal.
Stop use and consult a doctor if condition worsens, or symptoms last more than 7 days. Symptoms clear up and occur again within a few days.

KEEP OUT OF REACH OF CHILDREN

Keep out of the reach of children. If swallowed get medical help or contact a Poison Control Center right away

Directions

• Adults and children 2 years or older: apply to affected area not more than 3-4 times daily
• Children under 2 years of age: do not use, ask a doctor.

Inactive ingredients

Aloe Barbadensis Leaf Juice, Carthamus Tinctorius (Safflower) Seed Oil, Glycerin, Cetearyl Alcohol, Polysorbate 60, Microcrystalline Cellulose, Algin, Glyceryl Stearate, Sorbitan Caprylate, Propanediol, Benzoic Acid, Euphorbia Cerifera (Candelilla) Wax, Tocopheryl Acetate, Fragrance, Triethanolamine

NEW!

Lidocaine Lotion with Aloe Vera

Instant Maximum Relief For Severe Sunburns

Distributed by Hunters Beach Life,
1707 State Ave., Holly Hill, FL 32117
www.HUNTERBEACH.com
Made in the U.S.A.